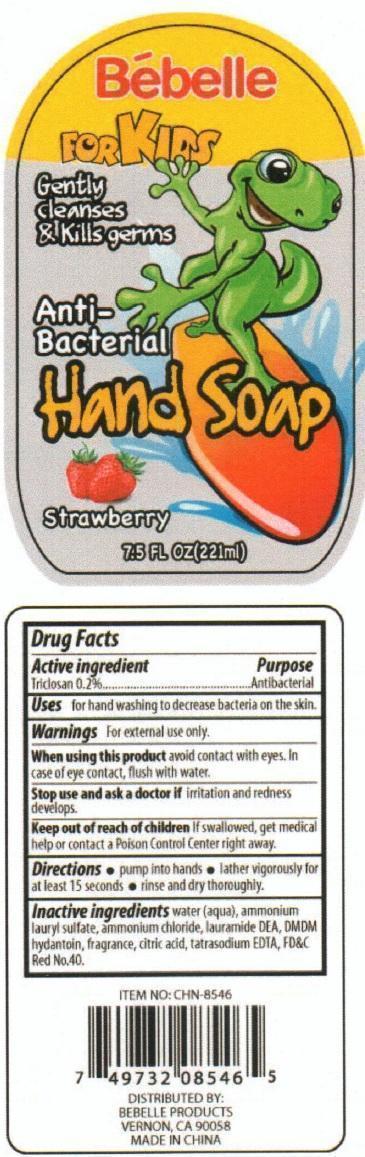 DRUG LABEL: Bebelle for Kids Antibacterial Hand
NDC: 50523-546 | Form: SOAP
Manufacturer: Volume Distributors, Inc.
Category: otc | Type: HUMAN OTC DRUG LABEL
Date: 20150904

ACTIVE INGREDIENTS: TRICLOSAN 0.2 g/100 mL
INACTIVE INGREDIENTS: WATER; AMMONIUM LAURYL SULFATE; AMMONIUM CHLORIDE; LAURIC DIETHANOLAMIDE; DMDM HYDANTOIN; CITRIC ACID MONOHYDRATE

Bebelle for Kids Antibacterial Hand Soap Strawberry

Active Ingredient

Triclosan 0.2%

Purpose

Antibacterial

Uses:

for hand washing to decrease bacteria on the skin.

Warnings for external use only.

When using this product avoid contact with eyes. In case of eye contact, flush with water.

Stop use and ask a doctor if irritation and redness develops.

Keep out of reach of children. If swallowed, get medical help or contact a Poison Control Center right away.

Directions

pump into hands

lather vigorously for at least 15 seconds

rinse and dry thoroughly.

Inactive Ingredients

Water (aqua), ammonium lauryl sulfate, ammonium chloride, lauramide DEA, DMDM hydantoin, fragrance, citric acid, tatrasodium EDTA, FD and C Red No. 40

PACKAGE LABEL

Bebelle

For Kids

Gently cleanses and kills germs

Antibacterial Hand Soap

Strawberry

Distributed by

Bebelle Products

Vernon, CA 90058

MADE IN CHINA